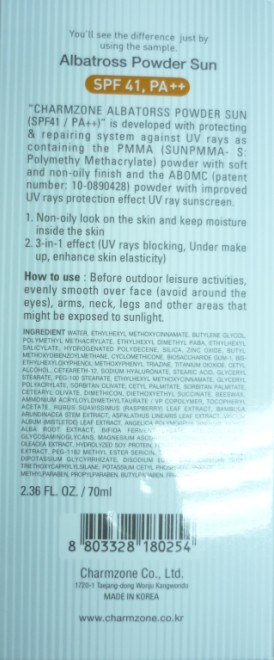 DRUG LABEL: Charmzone ALBATROSS Powder Sun (SPF41 PA)
NDC: 22201-2001 | Form: CREAM
Manufacturer: CHARMZONE CO LTD
Category: otc | Type: HUMAN OTC DRUG LABEL
Date: 20091109

ACTIVE INGREDIENTS: OCTINOXATE 4.91 mL/70 mL; OCTISALATE 3.15 mL/70 mL; ZINC OXIDE 2.33 mL/70 mL; TITANIUM DIOXIDE 1.225 mL/70 mL

KEEP OUT OF REACH OF CHILDREN

Label1

WARNINGS:

For external use only. Avoid contact with eyes. Keep out of children's reach.

ACTIVE INGREDIENT

Label2

INGREDIENTS:

WATER, ETHYLHEXYL METHOXYCINNAMATE, BUTYLENE GLYCOL, POLYMETHYL METHACRYLATE, ETHYLHEXYL DIMETHYL PABA, ETHYLHEXYL SALICYLATE, HYDROGENATED POLYDECENE, ZINC OXIDE, SILICA, CYCLOMETHICONE, BUTYL METHOXYDIBENZOYLMETHANE, BIOSACCHARIDE GUM-1, TITANIUM DIOXIDE, BIS-ETHYLHEXYLOXYPHENOL METHOXYPHENYL TRIAZINE, CETYL ALCOHOL, CETEARETH-12, GLYCERYL STEARATE, PEG-100 STEARATE, SODIUM HYALURONATE, STEARIC ACID, DIETHOXYETHYL SUCCINATE, GLYCERYL POLYACRYLATE, SORBITAN OLIVATE, BEESWAX, CETEARYL OLIVATE, CETYL PALMITATE, AMMONIUM ACRYLOYLDIMETHYLTAURATE / VP COPOLYMER, PHENOXYETHANOL, SORBITAN PALMITATE, TOCOPHERYL ACETATE, POTASSIUM CETYL PHOSPHATE, METHYLPARABEN, TRIETHOXYCAPRYLYLSILANE, FRAGRANCE, BIFIDA FERMENT LYSATE, BUTYLPARABEN, DIPOTASSIUM GLYCYRRHIZATE, HYDROLYZED SOY PROTEIN, MORUS ALBA ROOT EXTRACT, PEG-1182 METHYL ESTER SERICIN, PROPYLPARABEN, XANTHAN GUM, MAGNESIUM ASCORBYL PHOSPHATE, BHT, DIMETHICON, FOMES OFFICINALIS (MUSHROOM) EXTRACT, DISODIUM EDTA, STEARYL GLYCYRRHETINATE, GLYCOSAMINOGLYCANS, ATELOCOLLAGEN, BAMBUSA ARUNDINACEA STEM EXTRACT, RUBUS SUAVISSIMUS (RASPBERRY) LEAF EXTRACT, PORTULACA OLEACEA EXTRACT, ANGELICA POLYMORPHA SINENSIS ROOT EXTRACT, ASPALATHUS LINEARIS LEAF EXTRACT, VISCUM ALBUM (MISTLETOE) LEAF EXTRACT

WHEN USING

Label3

[How to Use]

1) Before outdoor leisure activities, evenly smooth over face (avoid around the eyes), arms, neck, legs and other areas that might be exposed to sunlight.

2) It can be used as under-makeup and helps the color makeup adhere to skin and stay on.

PACKAGE LABEL

Label4